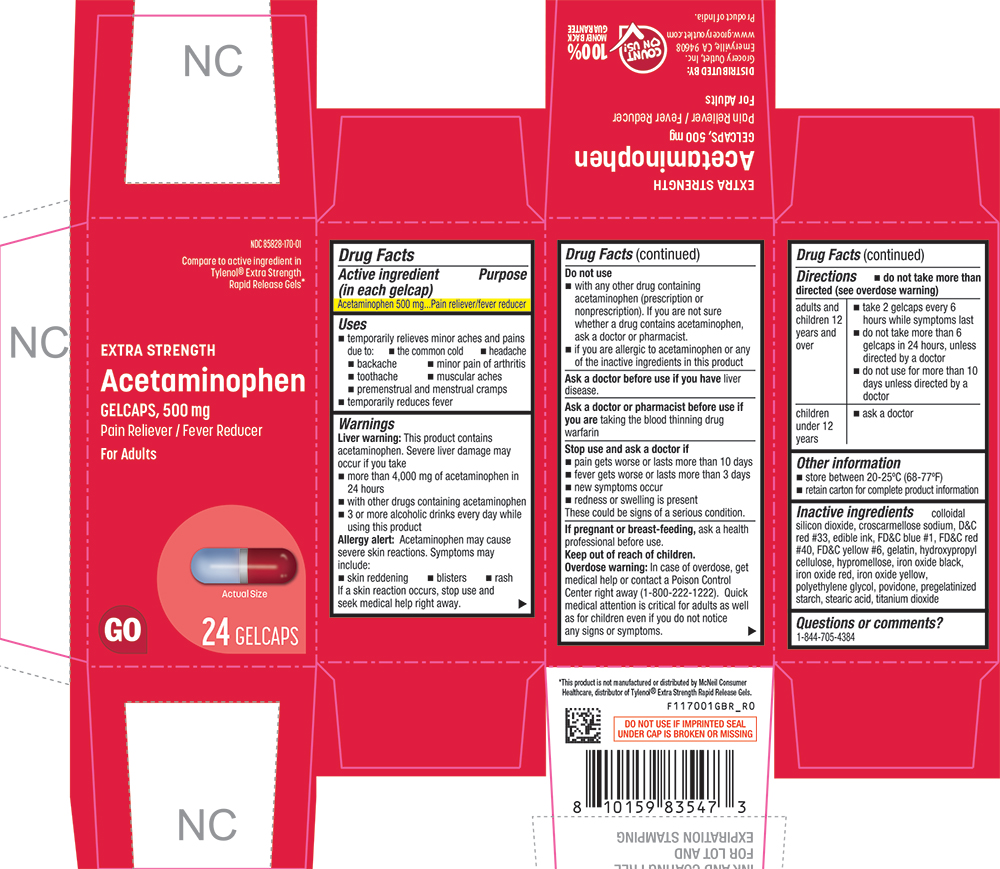 DRUG LABEL: Acetaminophen
NDC: 85828-170 | Form: TABLET, COATED
Manufacturer: Grocery Outlet, Inc.
Category: otc | Type: HUMAN OTC DRUG LABEL
Date: 20260218

ACTIVE INGREDIENTS: ACETAMINOPHEN 500 mg/1 1
INACTIVE INGREDIENTS: SILICON DIOXIDE; CROSCARMELLOSE SODIUM; D&C RED NO. 33; FD&C BLUE NO. 1; FD&C RED NO. 40; FD&C YELLOW NO. 6; GELATIN; HYDROXYPROPYL CELLULOSE (1600000 WAMW); HYPROMELLOSES; FERROSOFERRIC OXIDE; FERRIC OXIDE RED; FERRIC OXIDE YELLOW; POLYETHYLENE GLYCOL, UNSPECIFIED; POVIDONE, UNSPECIFIED; STARCH, PREGELATINIZED CORN; STEARIC ACID; TITANIUM DIOXIDE

1170-GBR-2026-0218

Drug Facts

Active ingredient (in each gelcap)

Acetaminophen 500 mg

Purpose

Pain reliever/fever reducer

Uses

- temporarily relieves minor aches and pains due to:
  - the common cold
  - headache
  - backache
  - minor pain of arthritis
  - toothache
  - muscular aches
  - premenstrual and menstrual cramps
- temporarily reduces fever

Warnings

Liver warning

This product contains acetaminophen. Severe liver damage may occur if you take

- more than 4,000 mg of acetaminophen in 24 hours
- with other drugs containing acetaminophen
- 3 or more alcoholic drinks every day while using this product

Allergy alert

acetaminophen may cause severe skin reactions. Symptoms may include:

- skin reddening
- blisters
- rash

If a skin reaction occurs, stop use and seek medical help right away.

Do not use

- with any other drug containing acetaminophen (prescription or nonprescription). If you are not sure whether a drug contains acetaminophen, ask a doctor or pharmacist.
- if you are allergic to acetaminophen or any of the inactive ingredients in this product

Ask a doctor before use if you haveliver disease.

Ask a doctor or pharmacist before use if you aretaking the blood thinning drug warfarin

Stop use and ask a doctor if

- pain gets worse or lasts more than 10 days
- fever gets worse or lasts more than 3 days
- new symptoms occur
- redness or swelling is present

These could be signs of a serious condition.

PREGNANCY OR BREAST FEEDING

If pregnant or breast-feeding,ask a health professional before use.

Keep out of reach of children.

Overdose warning

In case of overdose, get medical help or contact a Poison Control Center right away (1-800-222-1222). Quick medical attention is critical for adults as well as for children even if you do not notice any signs or symptoms.

Directions

- do not take more than directed (see overdose warning)

adults and children 12 years and over | - take 2 gelcaps every 6 hours while symptoms last - do not take more than 6 gelcaps in 24 hours, unless directed by a doctor - do not use for more than 10 days unless directed by a doctor
children under 12 years | - ask a doctor

Other information

- store between 20-25ºC (68-77ºF)
- retain carton for complete product information

Inactive ingredients

colloidal silicon dioxide, croscarmellose sodium, D&C red #33, edible ink, FD&C blue #1, FD&C red #40, FD&C yellow #6, gelatin, hydroxypropyl cellulose, hypromellose, iron oxide black, iron oxide red, iron oxide yellow, polyethylene glycol, povidone, pregelatinized starch, stearic acid, titanium dioxide

Questions or comments?

1-844-705-4384

PRINCIPAL DISPLAY PANEL

NDC 85828-170-01

Compare to the active ingredient in Tylenol® Extra Strength Rapid Release Gels*

EXTRA STRENGTH

Acetaminophen

GELCAPS, 500 mg

Pain Reliever / Fever Reducer

For Adults

Actual Size

GO

24 GELCAPS